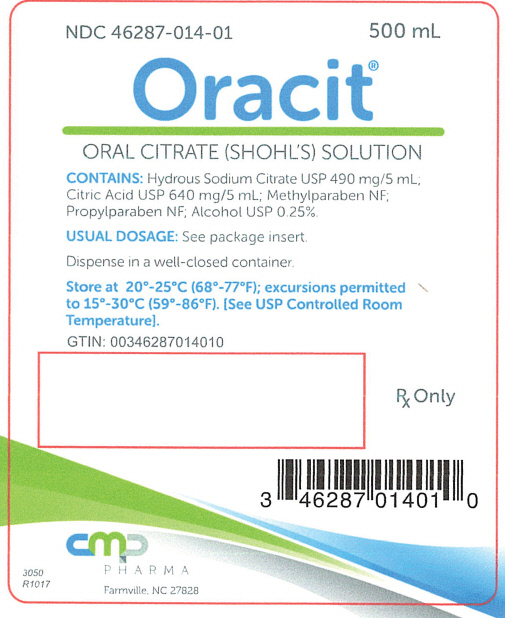 DRUG LABEL: Oracit
NDC: 46287-014 | Form: SOLUTION
Manufacturer: CMP Pharma, Inc.
Category: prescription | Type: HUMAN PRESCRIPTION DRUG LABEL
Date: 20231207

ACTIVE INGREDIENTS: CITRIC ACID MONOHYDRATE 640 mg/5 mL; TRISODIUM CITRATE DIHYDRATE 490 mg/5 mL
INACTIVE INGREDIENTS: ALCOHOL; METHYLPARABEN; PROPYLPARABEN

ORACIT®
Oral Citrate (Shohl's) Solution
CMP Pharma, Inc.

Rx Only

DESCRIPTION

The product is a clear, colorless solution containing Citric Acid USP 640 mg/5 mL, and Hydrous Sodium Citrate USP 490 mg/5 mL. It also contains Methylparaben NF and Propylparaben NF as preservatives. These concentrations yield 1 mEq of sodium, equivalent to 1 mEq of bicarbonate per mL of solution.

ACTION

Oral citrate solution is used as a systemic and urinary alkalinizer. Less than 5% of the citrate is excreted in the urine unchanged, since citrate oxidation is to a great extent complete.

INDICATIONS

ORACIT® is indicated for the treatment of metabolic acidosis. This solution is also useful in conditions where long term maintenance of alkaline urine is needed (e.g. uric acid and cystine calculi of the urinary tract). ORACIT® is also effective in treatment for acidosis of certain renal tubular disorders.

CONTRAINDICATIONS

ORACIT® is contraindicated in patients with severe renal impairment, oliguria or azotemia, untreated Addison's disease, adynamia episodica hereditaria, acute dehydration, heat cramp, anuria, severe myocardial damage, and hyperkalemia.

PRECAUTIONS

The citrate solution should be used with caution in patients with impaired renal function to avoid hypernatremia or alkalosis in the presence of hypocalcemia. Periodic determinations of serum electrolyte levels (especially bicarbonate levels) should be done in patients with renal disease to avoid cardiac failure, hypertension, peripheral and pulmonary edema, and toxemia of pregnancy. The solution should be diluted with water and preferably taken after meals to avoid saline laxative effects.

ADVERSE REACTIONS

Citrate solution is generally well tolerated when given in recommended doses when the patient has normal renal functions.

To report suspected adverse reactions, contact CMP Pharma, Inc., toll free at 1-844-321-1443 or the FDA at 1-800-FDA-1088 or www.fda.gov/medwatch.

DOSAGE AND ADMINISTRATION

The dose of ORACIT® is 10 to 30 mL, diluted with water, after meals and at bedtime. The dose should be titrated to achieve desired effects.

HOW SUPPLIED

ORACIT® is supplied in 500 mL bottles (NDC 46287-014-01), 30 mL unit dose bottles, 10 bottles per carton (NDC 46287-014-30), and 15 mL unit dose bottles, 10 bottles per carton (NDC 46287-014-15).

PHARMACIST

Dispense in well-closed containers.

STORAGE AND HANDLING

Store at 20°-25°C (68°-77°F); excursions permitted to 15°-30°C (59°-86°F). [See USP Controlled Room Temperature].

CMP Pharma, Inc.
Post Office Box 147
Farmville, North Carolina 27828

Revised December 2022
3082 R1222
Copyright © CMP Pharma, Inc. 2016

PRINCIPAL DISPLAY PANEL - 500 mL Bottle Label

NDC 46287-014-01
500 mL

Oracit®
ORAL CITRATE (SHOHL'S) SOLUTION

CONTAINS: Hydrous Sodium Citrate USP 490 mg/5 mL;
Citric Acid USP 640 mg/5 mL; Methylparaben NF;
Propylparaben NF; Alcohol USP 0.25%.

USUAL DOSAGE: See package insert.

Dispense in a well-closed container.

Store at 20°-25°C (68°-77°F); excursions permitted
to 15°-30°C (59°-86°F). [See USP Controlled Room
Temperature].

GTIN: 00346287014010

Rx Only

cmp
PHARMA
Farmville, NC 27828

3050
R1017